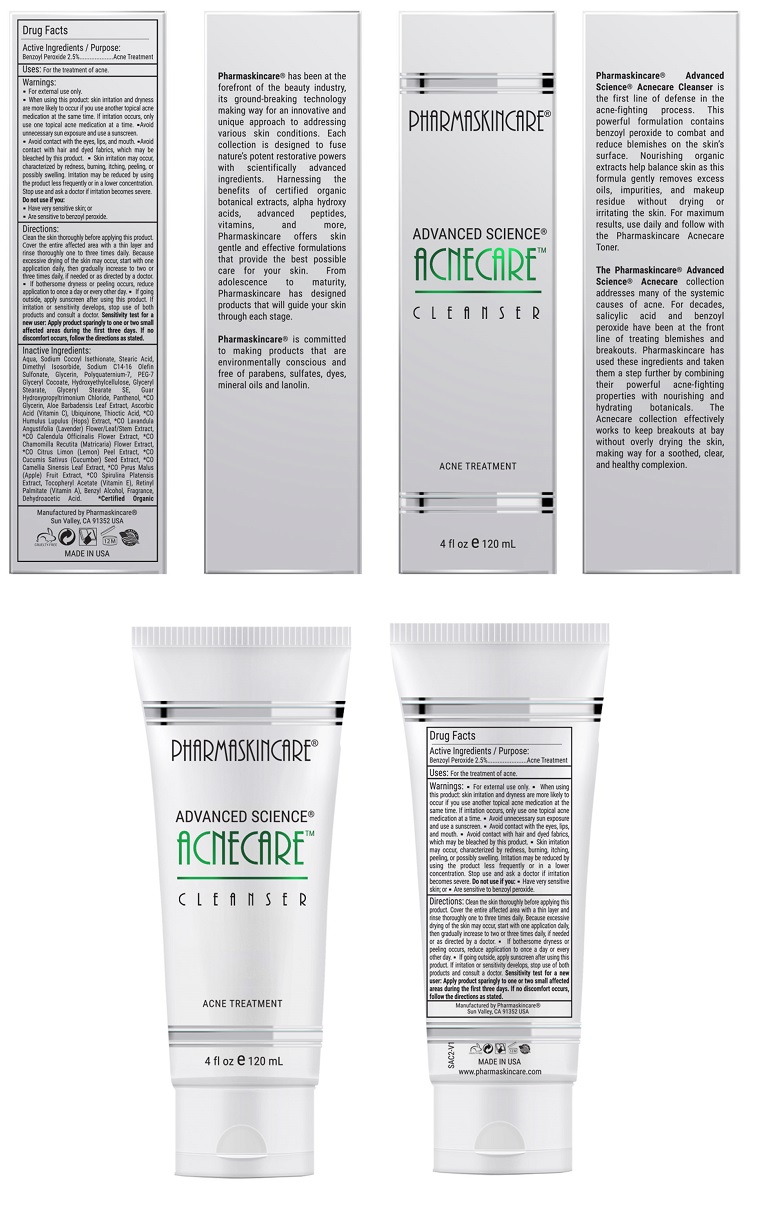 DRUG LABEL: Pharmaskincare Acnecare Cleanser
NDC: 68062-9107 | Form: SOLUTION
Manufacturer: Spa de Soleil
Category: otc | Type: HUMAN OTC DRUG LABEL
Date: 20171011

ACTIVE INGREDIENTS: BENZOYL PEROXIDE 0.063 mg/2.5 mL
INACTIVE INGREDIENTS: WATER; DIMETHYL ISOSORBIDE; SODIUM COCOYL ISETHIONATE; GLYCERIN; STEARIC ACID

Pharmaskincare Acnecare Cleanser

Active Ingredient

Benzoyl Peroxide 2.5%

Purpose

Acne Treatment

Warnings

- For external use only.
- When using this product : skin irritation and dryness is more likely to occur if you use another topical acne medication at the same time. If irritation occurs, only use one topical acne medication at a time.
- avoid unnecessary sun exposure and use a sunscreen
- avoid contact with the eyes, lips, and mouth
- avoid contact with hair and dyed fabrics, which may be bleached by this product
- skin irritation may occur, characterized by redness, burning, itching, peeling, or possibly swelling. Irritation may be reduced by using the product less frequently or in a lower concentration. Stop use and ask a doctor if irritation becomes severe

Do not use if you:

● have very sensitive skin

● are sensitive to benzoyl peroxide

Directions

Clean the skin thoroughly before applying this product. Cover the entire affected area with a thin layer and rinse thoroughly one to three times daily. Because excessive drying of the skin may occur, start with one application daily, then gradually increase to two or three times daily if needed or as directed by a doctor.

● If bothersome dryness or peeling occurs, reduce application to once a day or every other day.

● If going outside, apply sunscreen after using this product. If irritation or sensitivity develops, stop use of both products and ask a doctor.

Sensitivity Test for a New User. Apply product sparingly to one or two small affected areas during the first 3 days. If no discomfort occurs, follow the directions stated

Uses:

For the treatment of acne.

Inactive Ingredients:

Water, Sodium Cocoyl Isethionate, Stearic Acid, Dimethyl Isosorbide, Sodium C14-16 Olefin Sulfonate, Glycerin, Polyquaternium-7, Hydroxyethylcellulose, PEG-7 Glyceryl Cocoate, Glyceryl Stearate, Glyceryl Stearate SE, Guar Hydroxypropyltrimonium Chloride, Panthenol, Aloe Barbadensis Juice Extract, *CO Glycerin, Ascorbic Acid (Vitamin C), Thioctic Acid, Ubiquinone, *CO Humulus Lupulus (Hops) Extract, *CO Lavandula Angustifolia (Lavender) Flower/Leaf/Stem Extract, *CO Calendula Officinalis Flower Extract, *CO Chamomilla Recutita (Matricaria) Flower Extract, *CO Citrus Limon (Lemon) Peel Extract, *CO Cucumis Sativus (Cucumber) Seed Extract, *CO Camellia Sinensis Leaf Extract, *CO Pyrus Malus (Apple) Fruit Extract, *CO Spirulina Platensis Extract, Tocopheryl Acetate (Vitamin E), Retinyl Palmitate (Vitamin A), Phenoxyethanol, Ethylhexylglycerin, Fragrance

Warning

Keep out of reach of children.

Do not use if you:

● have very sensitive skin

● are sensitive to benzoyl peroxide

PACKAGE LABEL

Pharmaskincare Acnecare Cleanser.jpg